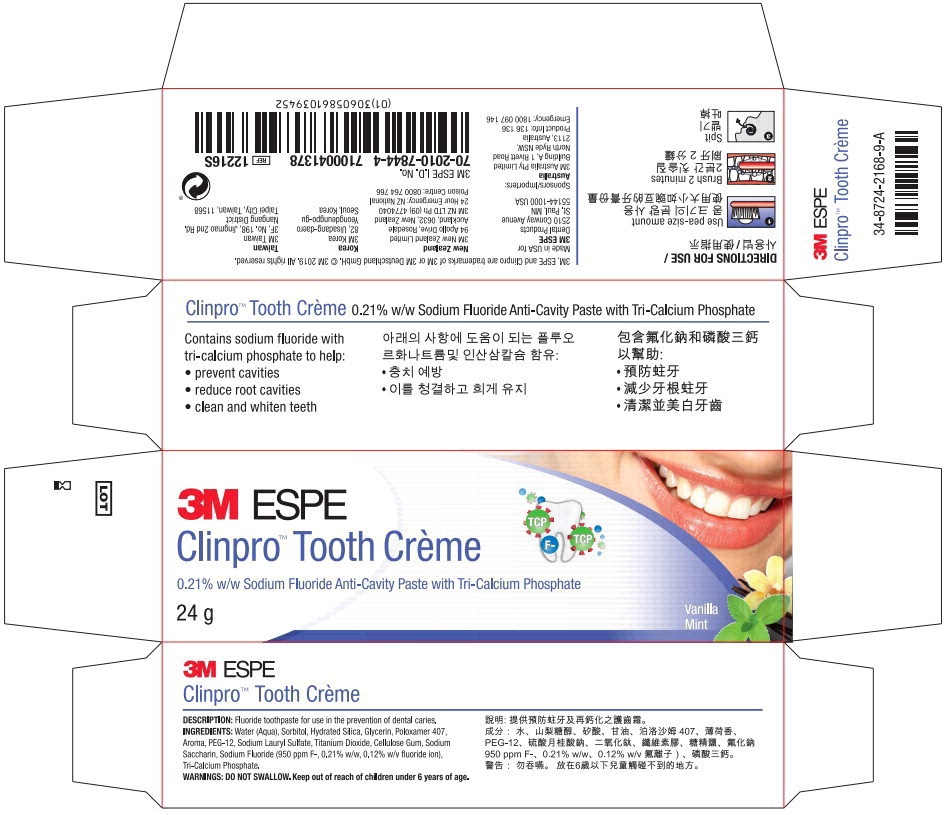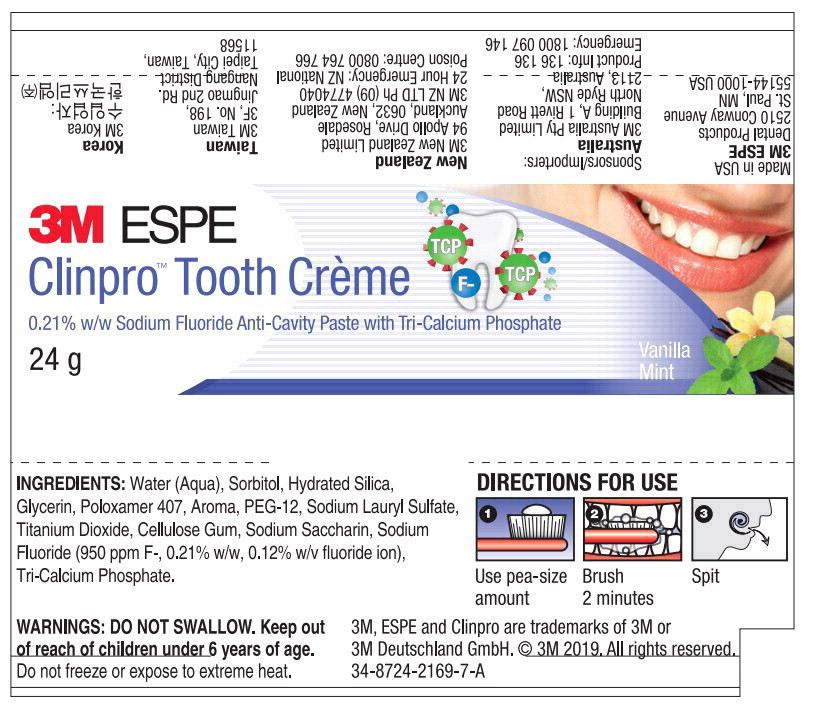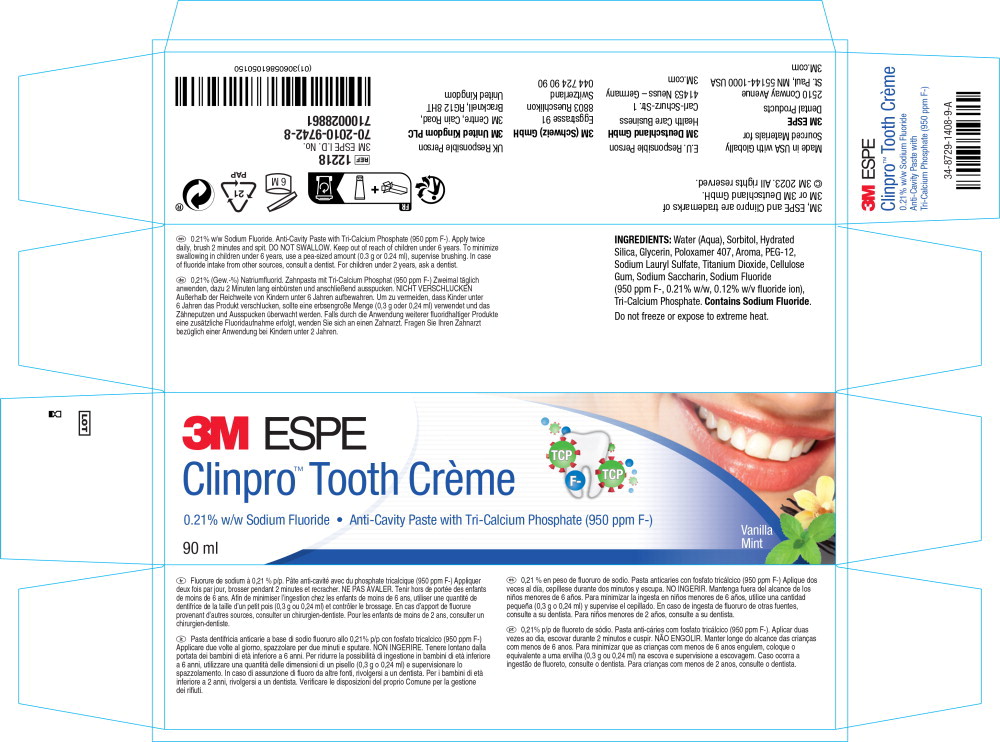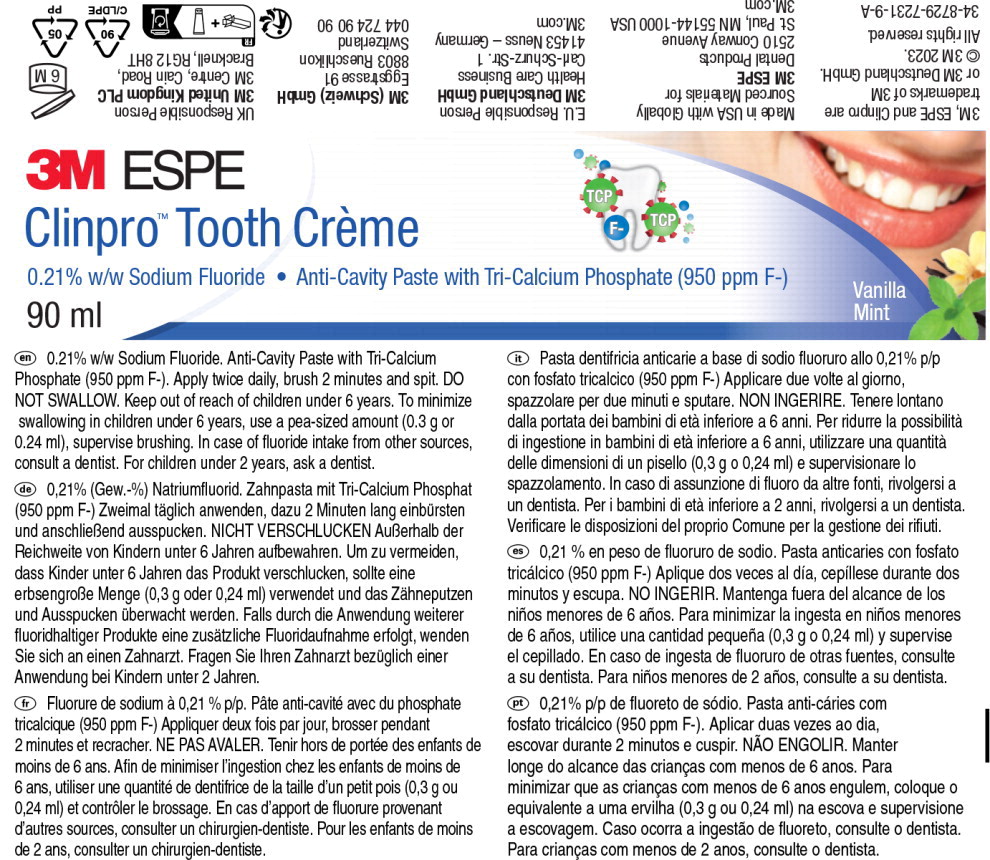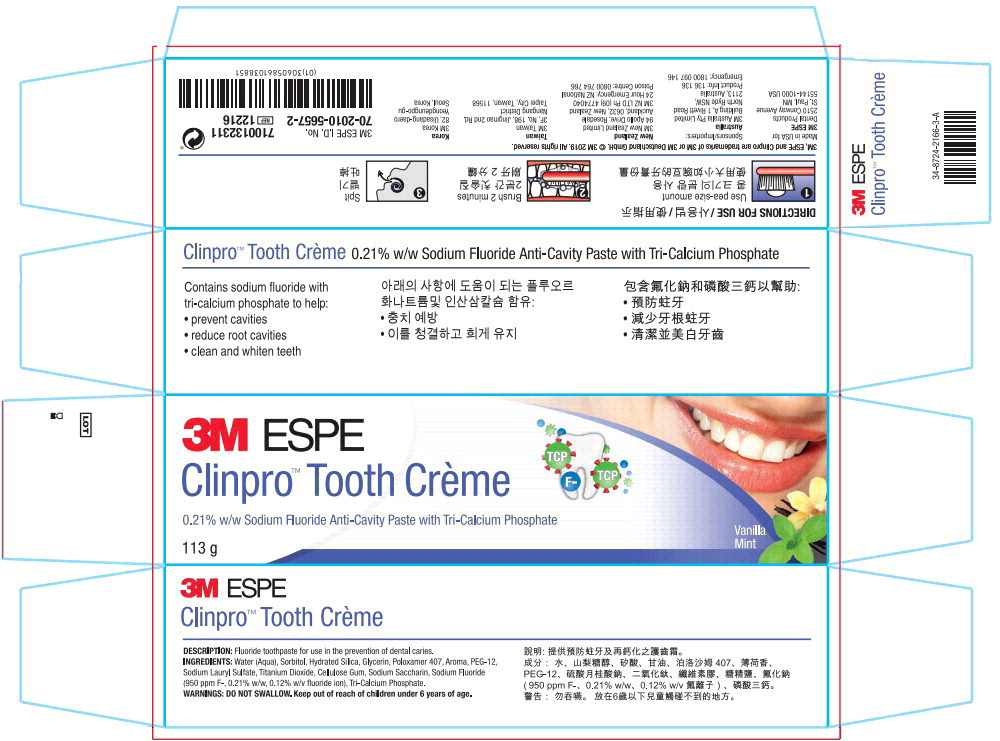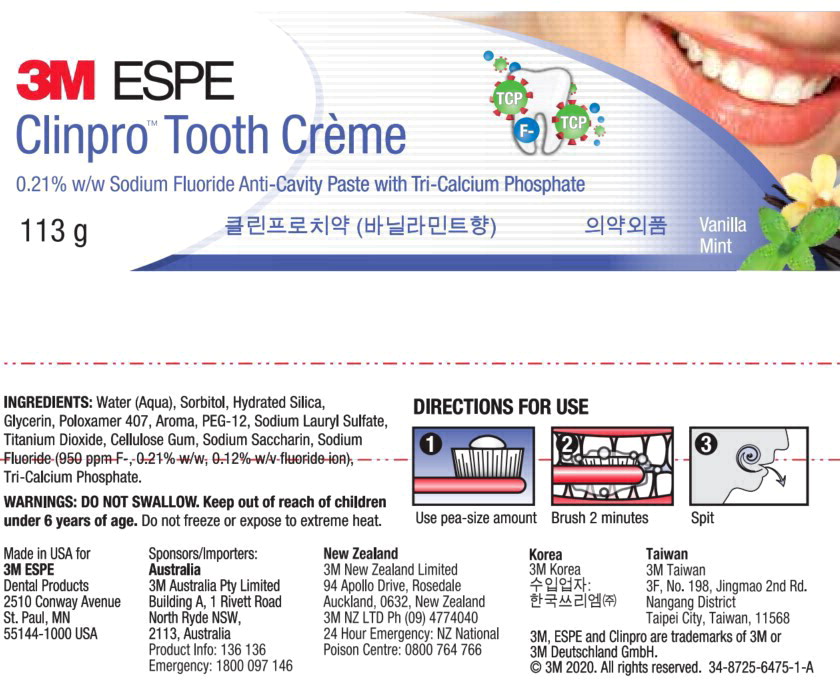 DRUG LABEL: Clinpro Tooth Creme
NDC: 48878-3150 | Form: PASTE, DENTIFRICE
Manufacturer: Solventum US LLC
Category: otc | Type: HUMAN OTC DRUG LABEL
Date: 20240801

ACTIVE INGREDIENTS: sodium fluoride 0.950 mg/1 g
INACTIVE INGREDIENTS: Water; Sorbitol; Silicon Dioxide; Glycerin; Polyethylene Glycol, Unspecified; Sodium Lauryl Sulfate; Titanium Dioxide; Carboxymethylcellulose Sodium; Saccharin Sodium; Tricalcium Phosphate

Principal Display Panel - 24g Carton Label

3M ESPE

Clinpro™ Tooth Crème

0.21% w/w Sodium Fluoride Anti-Cavity Paste with Tri-Calcium Phosphate

24g

Vanilla Mint

Principal Display Panel – 24g Tube Label

3M ESPE

Clinpro™ Tooth Crème

0.21% w/w Sodium Fluoride Anti-Cavity Paste with Tri-Calcium Phosphate

24g

Vanilla Mint

Principal Display Panel - 90 mL Carton Label

3M ESPE

Clinpro™ Tooth Crème

0.21% w/w Sodium Fluoride Anti-Cavity Paste with Tri-Calcium Phosphate (950 ppm F-)

90 ml

Vanilla Mint

Principal Display Panel - 90 mL Tube Label

3M ESPE

Clinpro™ Tooth Crème

0.21% w/w Sodium Fluoride Anti-Cavity Paste with Tri-Calcium Phosphate (950 ppm F-)

90 ml

Vanilla Mint

Principal Display Panel - 113g Carton Label

3M ESPE

Clinpro™ Tooth Crème

0.21% w/w Sodium Fluoride Anti-Cavity Paste with Tri-Calcium Phosphate

113g

Vanilla Mint

Principal Display Panel - 113g Tube Label

3M ESPE

Clinpro™ Tooth Crème

0.21% w/w Sodium Fluoride Anti-Cavity Paste with Tri-Calcium Phosphate

113g

Vanilla Mint